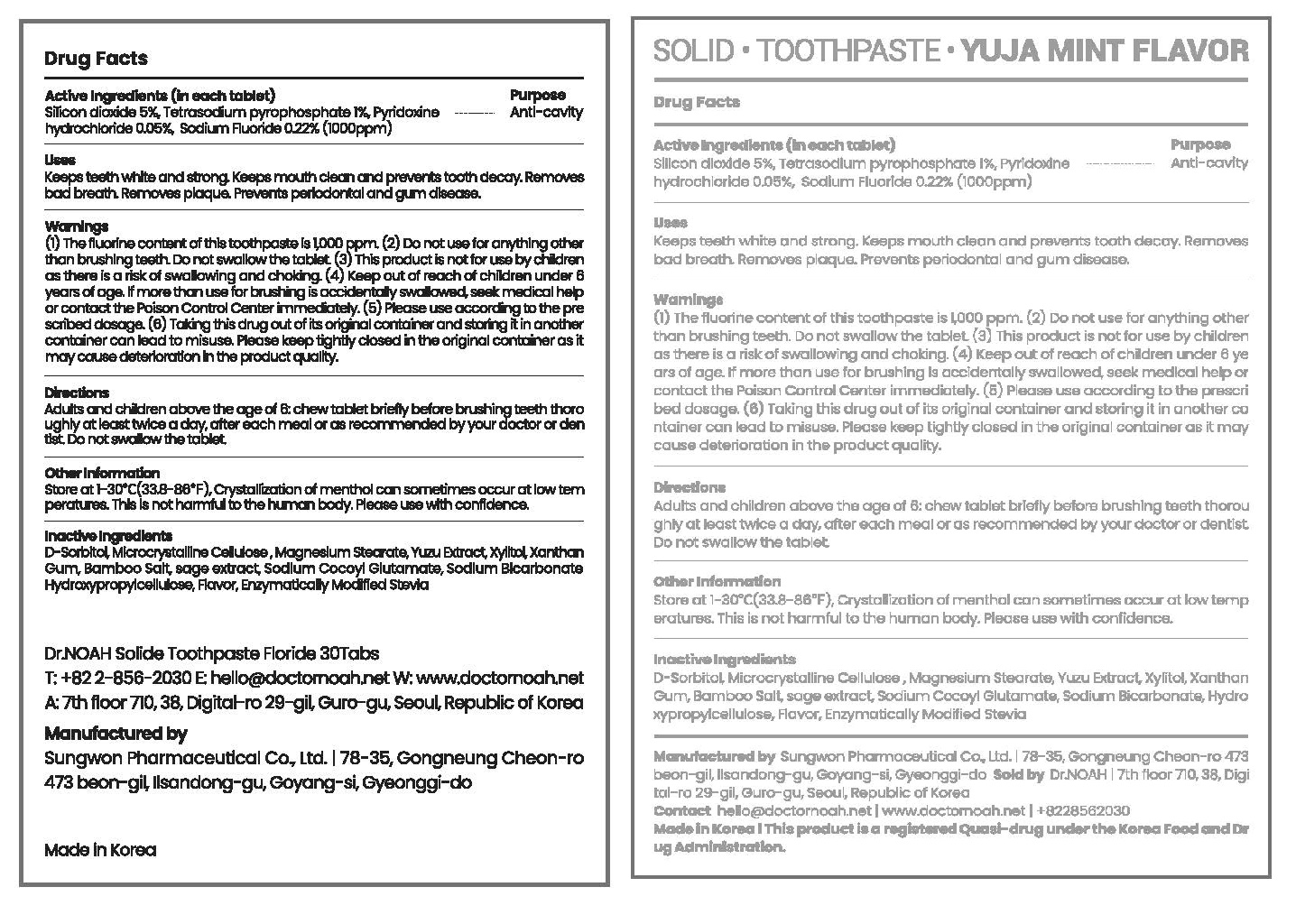 DRUG LABEL: Dr.NOAH SOLIDTOOTHPASTE
NDC: 82359-0003 | Form: TABLET
Manufacturer: DR.Noah
Category: otc | Type: HUMAN OTC DRUG LABEL
Date: 20211029

ACTIVE INGREDIENTS: SODIUM FLUORIDE 0.00154 g/1 1; SILICON DIOXIDE 0.035 g/1 1; SODIUM PYROPHOSPHATE 0.007 g/1 1; PYRIDOXINE HYDROCHLORIDE 0.00035 g/1 1
INACTIVE INGREDIENTS: SODIUM BICARBONATE; SORBITOL

ACTIVE INGREDIENT

Silicon Dioxide, Tetrasodium Pyrophosphate, Pyridoxine Hydrochloride, Sodium Fluoride

INACTIVE INGREDIENT

D-Sorbitol,Microcrystalline Cellulose, Xylitol, Enzymatically Modified Stevia, Bamboo Salt, L-Menthol, CombinedFlavor(Coolmint Flavor Powder), Combined Flavor(Lemon Flavor Powder), Combined Flavor(SperamintFlavor Powder), Yuzu Extract, Chamomile Powder, Sodium Bicarbonate, Xanthan Gum,Hydroxypropylcellulose, Magnesium Stearate, Sodium Cocoyl Glutamate

PURPOSE

■ Keeps teeth white and strong

■ Keep the oral cavity clean

■ Prevents tooth decay and bad breath caused by fluoride

■ Removing plaque, preventing gingivitis and periodontitis

■ Periodontal Disease Prevention

■ Gum Disease Prevention

KEEP OUT OF REACH OF CHILDREN

WARNING

For oral use only
When using this product

■ Do not use other than brushing teeth and be careful not to swallow

Keep out of reach of children

■ if swallowed, seek medical help or contact the poison control center immediately

USES

for oral use only

INDICATION & USAGE SECTION

adults and children above the age of 6: chew tablet briefly before brushing teeth thoroughly at least twice a day, after each meal or as recommended by your doctor or dentist

do not swallow the tablet